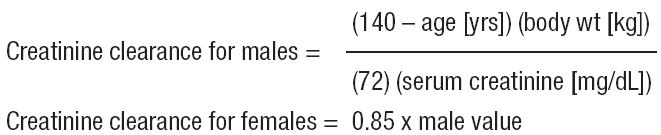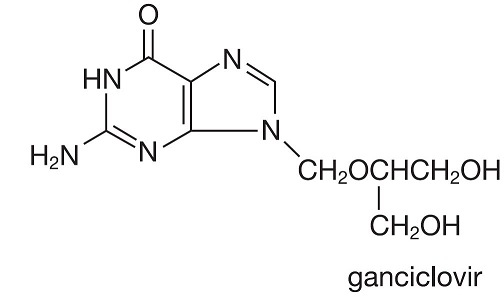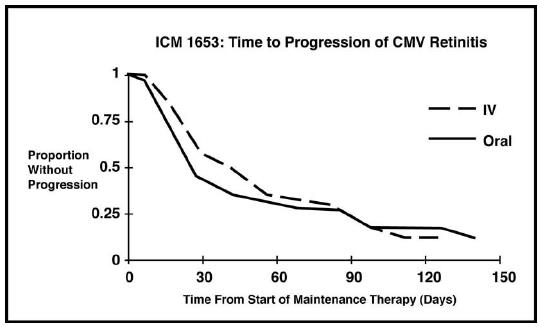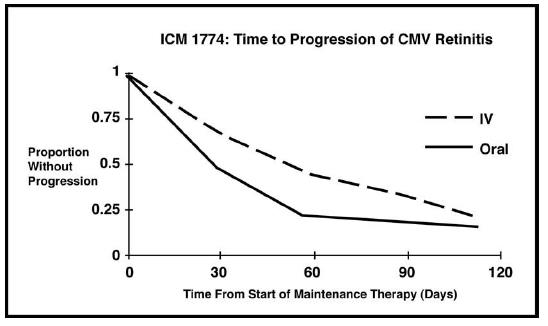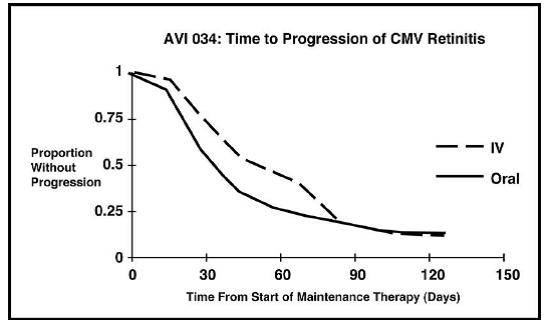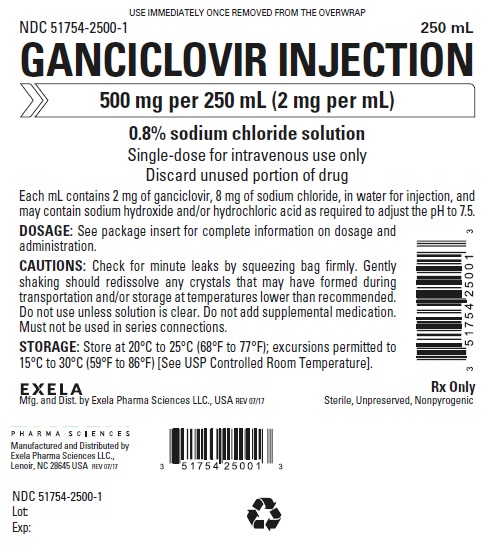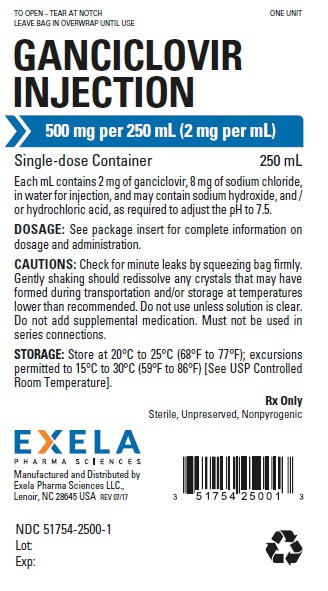 DRUG LABEL: GANCICLOVIR
NDC: 51754-2500 | Form: INJECTION, SOLUTION
Manufacturer: EXELA PHARMA SCIENCES, LLC
Category: prescription | Type: HUMAN PRESCRIPTION DRUG LABEL
Date: 20171006

ACTIVE INGREDIENTS: GANCICLOVIR 2 mg/1 mL
INACTIVE INGREDIENTS: SODIUM CHLORIDE 8 mg/1 mL; SODIUM HYDROXIDE; HYDROCHLORIC ACID

HIGHLIGHTS OF PRESCRIBING INFORMATION

These highlights do not include all the information needed to use GANCICLOVIR INJECTION safely and effectively. See full prescribing information for GANCICLOVIR INJECTION.
GANCICLOVIR INJECTION, for intravenous use
Initial U.S. Approval: 1989

WARNING: HEMATALOGIC TOXICITY, IMPAIRMENT OF FERTILITY, TERATOGENICITY, and CARCINOGENICITY

See full prescribing information for complete boxed warning.

- Hematologic Toxicity: Granulocytopenia, anemia, thrombocytopenia, and pancytopenia have been reported in patients treated with ganciclovir. (5.1)
- Impairment of Fertility: Based on animal data, GANCICLOVIR INJECTION may cause temporary or permanent inhibition of spermatogenesis in males and suppression of fertility in females. (5.2)
- Fetal Toxicity: Based on animal data, GANCICLOVIR INJECTION has the potential to cause birth defects in humans. (5.3)
- Mutagenesis and Carcinogenesis: Based on animal data, GANCICLOVIR INJECTION has the potential to cause cancer in humans. (5.4)

1 INDICATIONS AND USAGE

GANCICLOVIR INJECTION is a nucleoside analogue CMV DNA polymerase inhibitor indicated for the:

- Treatment of CMV retinitis in immunocompromised adult patients, including patients with acquired immunodeficiency syndrome (AIDS). (1.1)
- Prevention of CMV disease in adult transplant recipients at risk for CMV disease. (1.2)

2 DOSAGE AND ADMINISTRATION

Dosage in Adult Patients with Normal Renal Function (2.3, 2.4)
Treatment of CMV retinitis (2.3) | Induction: 5 mg/kg (given intravenously at a constant rate over 1 hour) every 12 hours for 14 to 21 days.; Maintenance: 5 mg/kg (given intravenously at a constant rate over 1 hour) once daily for 7 days per week, or 6 mg/kg once daily for 5 days per week.
Prevention of CMV disease in transplant recipients (2.4) | Induction: 5 mg/kg (given intravenously at a constant rate over 1 hour) every 12 hours for 7 to 14 days.; Maintenance: 5 mg/kg (given intravenously at a constant rate over 1 hour) once daily for 7 days per week, or 6 mg/kg once daily for 5 days per week until 100 to 120 days post-transplantation.

- Adult patients with renal impairment: Adjust dosage based on creatinine clearance. (2.5)

3 DOSAGE FORMS AND STRENGTHS

Injection: 500 mg ganciclovir in 250 mL (2 mg per mL) solution in a single-dose bag for intravenous use. (3)

4 CONTRAINDICATIONS

Hypersensitivity to ganciclovir, valganciclovir or acyclovir. (4)

5 WARNINGS AND PRECAUTIONS

- Hematologic toxicity: Granulocytopenia (neutropenia), anemia, thrombocytopenia, and pancytopenia have been reported with use of ganciclovir. Avoid the use of GANCICLOVIR INJECTION if absolute neutrophil count is less than 500 cells/µL, hemoglobin is less than 8 g/dL, or platelet count is less than 25,000 cells/µL. Use with caution in patients with pre-existing cytopenias or in patients receiving myelosuppressive drugs or irradiation. Monitor with frequent complete blood and platelet counts. (5.1)
- Impairment of renal function: Increased serum creatinine levels have been observed with the use of ganciclovir, particularly in elderly patients and transplant patients receiving concomitant nephrotoxic drugs. Monitor renal function during therapy with GANCICLOVIR INJECTION, particularly in elderly patients and in patients taking other nephrotoxic drugs, and reduce dosage in patients with renal impairment. (5.2)
- Impairment of fertility: Based on animal studies, GANCICLOVIR INJECTION may cause temporary or permanent female and male infertility. (5.3)
- Fetal toxicity: Based on findings in animal studies, GANCICLOVIR INJECTION may cause fetal toxicity. Females of reproductive potential should use effective contraception during treatment and for at least 30 days following treatment with GANCICLOVIR INJECTION. Males should practice barrier contraception during treatment and for at least 90 days following treatment with GANCICLOVIR INJECTION. (5.4)
- Mutagenicity and carcinogenicity: Based on animal studies, GANCICLOVIR INJECTION is potentially mutagenic and carcinogenic. (5.5)

6 ADVERSE REACTIONS

Most common adverse reactions and laboratory abnormalities reported in at least 20% of patients were fever, diarrhea, leukopenia, anemia, catheter-related events (including catheter infection and catheter sepsis), and elevated creatinine levels. (6.1)

To report SUSPECTED ADVERSE REACTIONS, Contact Exela Pharma Sciences, LLC at 1-888-451-4321 or FDA at 1-800-FDA-1088 or www.fda.gov/medwatch.

7 DRUG INTERACTIONS

- Didanosine: Patients should be closely monitored for didanosine toxicity. (7)
- Zidovudine: Potential to cause neutropenia and anemia. Monitor with frequent tests of white blood cell counts with differential and hemoglobin levels. (7)
- Probenecid: Ganciclovir dose may need to be reduced. Monitor for evidence of ganciclovir toxicity. (7)
- Imipenem-cilastatin: Generalized seizures have been reported in patients with concomitant use of ganciclovir and imipenem-cilastatin. (7)
- Cyclosporine or amphotericin B: Monitor renal function. (5.2, 7)
- Drugs such as dapsone, pentamidine, flucytosine, vincristine, vinblastine, adriamycin, amphotericin B, trimethoprim/sulfamethoxazole combinations or other nucleoside analogues should be considered for concomitant use with ganciclovir only if the potential benefits are judged to outweigh the risks. (7)

8 USE IN SPECIFIC POPULATIONS

Lactation: Breastfeeding is not recommended. (8.2)

FULL PRESCRIBING INFORMATION

WARNING: HEMATALOGIC TOXICITY, IMPAIRMENT OF FERTILITY, TERATOGENICITY, and CARCINOGENICITY

- Hematologic Toxicity: Granulocytopenia, anemia, thrombocytopenia, and pancytopenia have been reported in patients treated with ganciclovir [see Warnings and Precautions (5.1)].
- Impairment of Fertility: Based on animal data, GANCICLOVIR INJECTION may cause temporary or permanent inhibition of spermatogenesis in males and suppression of fertility in females [see Warnings and Precautions (5.3)].
- Fetal Toxicity: Based on animal data, GANCICLOVIR INJECTION has the potential to cause birth defects in humans [see Warnings and Precautions (5.4)].
- Mutagenesis and Carcinogenesis: Based on animal data, GANCICLOVIR INJECTION has the potential to cause cancer in humans [see Warnings and Precautions (5.5)].

1 INDICATIONS AND USAGE

1.1 Treatment of CMV Retinitis

GANCICLOVIR INJECTION is indicated for the treatment of cytomegalovirus (CMV) retinitis in immunocompromised adult patients, including patients with acquired immunodeficiency syndrome (AIDS) [see Clinical Studies (14)].

1.2 Prevention of CMV Disease in Transplant Recipients

GANCICLOVIR INJECTION is indicated for the prevention of CMV disease in adult transplant recipients at risk for CMV disease [see Clinical Studies (14)].

2 DOSAGE AND ADMINISTRATION

2.1 Important Dosing and Administration Information

- Do not administer GANCICLOVIR INJECTION by rapid or bolus intravenous injection which may increase toxicity as a result of excessive plasma levels.
- The recommended dosage and infusion rate for GANCICLOVIR INJECTION should not be exceeded.
- Administration of GANCICLOVIR INJECTION should be accompanied by adequate hydration.
- GANCICLOVIR INJECTION should only be infused into veins with adequate blood flow to permit rapid dilution and distribution.
- Parenteral drug products should be inspected visually for particulate matter and discoloration prior to administration, whenever solution and container permit.

2.2 Testing Before and During Treatment

- Females of reproductive potential should undergo pregnancy testing before initiation of GANCICLOVIR INJECTION [see Warnings and Precautions (5.4), Use in Specific Populations (8.1, 8.3)].
- Complete blood counts with differential and platelet counts should be performed frequently, especially in patients in whom ganciclovir or other nucleoside analogues have previously resulted in cytopenias, or in whom absolute neutrophil counts are less than 1000 cells/μL at the beginning of treatment [see Warnings and Precautions (5.1)].
- All patients should be monitored for renal function before and during treatment with GANCICLOVIR INJECTION and dosage should be adjusted as needed [see Dosage and Administration (2.5), Warnings and Precautions (5.2)].

Patients with CMV retinitis should have frequent ophthalmological examinations during treatment with GANCICLOVIR INJECTION to monitor disease status and for other retinal abnormalities [see Adverse Reactions (6.1)].

2.3 Recommended Dosage for Treatment of CMV Retinitis in Adult Patients with Normal Renal Function

Induction Dosage: The recommended initial dosage of GANCICLOVIR INJECTION for patients with normal renal function is 5 mg/kg (given intravenously at a constant rate over 1 hour) every 12 hours for 14 to 21 days.

Maintenance Dosage: Following induction treatment, the recommended maintenance dosage of GANCICLOVIR INJECTION is 5 mg/kg (given intravenously at a constant rate over 1 hour) once daily for 7 days per week, or 6 mg/kg once daily for 5 days per week.

2.4 Recommended Dosage for Prevention of CMV Disease in Adult Transplant Recipients with Normal Renal Function

Induction Dosage:The recommended initial dosage of GANCICLOVIR INJECTION for patients with normal renal function is 5 mg/kg (given intravenously at a constant rate over 1 hour) every 12 hours for 7 to 14 days.

Maintenance Dosage: Following induction, the recommended maintenance dosage of GANCICLOVIR INJECTIONS is 5 mg/kg (given intravenously at a constant rate over 1 hour) once daily for 7 days per week, or 6 mg/kg once daily for 5 days per week until 100 to 120 days post-transplantation.

2.5 Recommended Dosage in Adult Patients with Renal Impairment

For patients with renal impairment, refer to Table 1 for recommended doses of GANCICLOVIR INJECTION for induction and maintenance dosage for treatment of CMV retinitis and prevention of CMV disease in transplant patients. Monitor serum creatinine or creatinine clearance during treatment to allow for dosage adjustments in patients with impaired renal function.

Table 1. Recommended Induction and Maintenance Dosage for Adult Patients with Renal Impairment
Creatinine Clearance* (mL/min) | GANCICLOVIR INJECTION Induction Dose (mg/kg) | Dosing Interval (hours) for Induction | GANCICLOVIR INJECTION Maintenance Dose (mg/kg) | Dosing Interval (hours) for Maintenance
Greater than or equal to 70 | 5 | 12 | 5 | 24
50-69 | 2.5 | 12 | 2.5 | 24
25-49 | 2.5 | 24 | 1.25 | 24
10-24 | 1.25 | 24 | 0.625 | 24
Less than 10 | 1.25 | 3 times per week, following hemodialysis | 0.625 | 3 times per week, following hemodialysis

* Creatinine clearance can be related to serum creatinine by the formulas given below:

Dosing for patients undergoing hemodialysis should not exceed 1.25 mg per kg 3 times per week,

following each hemodialysis session. GANCICLOVIR INJECTION should be given shortly after completion of the hemodialysis session, since hemodialysis has been shown to reduce plasma levels by approximately 50% [see Clinical Pharmacology (12.3)].

2.6 Handling and Disposal

Because ganciclovir shares some of the properties of antitumor agents (i.e., carcinogenicity and mutagenicity), procedures for proper handling and disposal for cytotoxic drugs should be considered^1 [see How Supplied/Storage and Handling (16)]. The premix flexible plastic container bag contains no preservative; therefore, any unused portion should be discarded after each use.

3 DOSAGE FORMS AND STRENGTHS

Injection: 500 mg of ganciclovir in 250 mL (2 mg per mL) sterile, unpreserved, colorless solution in a single-dose bag for intravenous use.

4 CONTRAINDICATIONS

GANCICLOVIR INJECTION is contraindicated in patients who have experienced a clinically significant hypersensitivity reaction (e.g., anaphylaxis) to ganciclovir, valganciclovir or acyclovir.

5 WARNINGS AND PRECAUTIONS

5.1 Hematologic Toxicity

Granulocytopenia (neutropenia), anemia,thrombocytopenia, and pancytopenia have been observed in patients treated with ganciclovir. The frequency andseverity of these events vary widely in different patient populations [see Adverse Reactions (6.1)]. GANCICLOVIR INJECTION is not recommended if the absolute neutrophil count is less than 500 cells/μL, hemoglobin is less than 8 g/dL, or the platelet count is less than 25,000 cells/μL. GANCICLOVIR INJECTION should also be used with caution in patients with pre-existing cytopenias and in patients receiving myelosuppressive drugs or irradiation. Neutropenia usually occurs during the first or second week of treatment but may occur at any time during treatment. Cell counts usually begin to recover within 3 to 7 days after discontinuing drug. Colony-stimulating factors have been shown to increase neutrophil and white blood cell counts in patients receiving ganciclovir for treatment of CMV retinitis.

Due to the frequency of neutropenia, anemia and thrombocytopenia in patients receiving GANCICLOVIR INJECTION, complete blood counts with differential and platelet counts should be performed frequently, especially in patients in whom ganciclovir or other nucleoside analogues have previously resulted in leukopenia, or in whom neutrophil counts are less than 1000 cells/µL at the beginning of treatment [see Dosage and Administration (2.2)].

5.2 Impairment of Renal Function

Increased serum creatinine levels have been reported in elderly patients and in transplant patients receiving concomitant nephrotoxic medications (i.e., cyclosporine and amphotericin B). Monitoring renal function during therapy with GANCICLOVIR INJECTION is essential, especially for elderly patients and those patients receiving concomitant agents that may cause nephrotoxicity [see Dosage and Administration (2.5), Use in Specific Populations (8.5)].

5.3 Impairment of Fertility

Based on animal data, GANCICLOVIR INJECTION at the recommended human dose (RHD) may cause temporary or permanent inhibition of spermatogenesis in males, and may cause suppression of fertility in females. Advise patients that fertility may be impaired with use of GANCICLOVIR INJECTION [see Use in Specific Population (8.1), Nonclinical Toxicology (13.1)].

5.4 Fetal Toxicity

GANCICLOVIR INJECTION may cause fetal toxicity when administered to pregnant women based on findings in animal studies. Systemic exposure of ganciclovir in animals at approximately 2 times the RHD caused fetal growth retardation, embryolethality, teratogenicity, and/or maternal toxicity. Teratogenic changes in animals included cleft palate, anophthalmia/microphthalmia, aplastic organs (kidney and pancreas), hydrocephaly and brachygnathia. Women of childbearing potential should be advised to use effective contraception during treatment and for at least 30 days following treatment with GANCICLOVIR INJECTION. Similarly, men should be advised to practice barrier contraception during and for at least 90 days following treatment with GANCICLOVIR INJECTION [see Use in Specific Populations (8.1, 8.3), Nonclinical Toxicology (13.1)].

5.5 Mutagenesis and Carcinogenesis

Animal data indicate that ganciclovir is mutagenic and carcinogenic. GANCICLOVIR INJECTION should therefore be considered a potential carcinogen in humans [see Dosage and Administration (2.6), Nonclinical Toxicology (13.1)].

6 ADVERSE REACTIONS

The following adverse reactions are discussed in other sections of the labeling:

- Hematologic Toxicity [see Warnings and Precautions (5.1)]
- Impairment of Renal Function [see Warnings and Precautions (5.2)]
- Impairment of Fertility [see Warnings and Precautions (5.3)]
- Fetal Toxicity [see Warnings and Precautions (5.4)]
- Mutagenesis and Carcinogenesis [see Warnings and Precautions (5.5)]

6.1 Clinical Trials Experience

Because clinical trials are conducted under widely varying conditions, adverse reaction rates observed in the clinical trials of a drug cannot be directly compared to rates in the clinical trials of another drug and may not reflect the rates observed in practice.

Adverse Reactions in Patients with CMV Retinitis
Three controlled, randomized, phase 3 trials comparing intravenous ganciclovir and ganciclovir capsules for maintenance treatment of CMV retinitis have been completed. During these trials, 9% of subjects were prematurely discontinued because of adverse reactions. Selected adverse reactions and laboratory abnormalities reported during the conduct of these controlled trials are summarized in Table 2 and Table 3, respectively [see Clinical Studies (14)].

Table 2. Pooled Selected Adverse Events Reported in ≥ 5% of Subjects Comparing Intravenous Ganciclovir to Ganciclovir Capsules for Maintenance Treatment of CMV Retinitis
Adverse Event | Maintenance Treatment Studies
Adverse Event | Intravenous Ganciclovir (n=179) | Ganciclovir Capsules (n=326)
Fever | 48% | 38%
Diarrhea | 44% | 41%
Leukopenia | 41% | 29%
Anemia | 25% | 19%
Total catheter events: | 22% | 6%
Catheter infection | 9% | 4%
Catheter sepsis | 8% | 1%
Other catheter related events | 5% | 1%
Sepsis | 15% | 4%
Anorexia | 14% | 15%
Vomiting | 13% | 13%
Infection | 13% | 9%
Sweating | 12% | 11%
Chills | 10% | 7%
Neuropathy | 9% | 8%
Thrombocytopenia | 6% | 6%
Pruritus | 5% | 6%

Retinal Detachment

Retinal detachment has been observed in subjects with CMV retinitis both before and after initiation of therapy with ganciclovir. Its relationship to therapy with ganciclovir is unknown. Retinal detachment occurred in 11% of patients treated with intravenous ganciclovir and in 8% of patients treated with ganciclovir capsules.

Table 3. Selected Laboratory Abnormalities in Trials for Treatment of CMV Retinitis
Laboratory Abnormalities | CMV Retinitis Treatment*
Laboratory Abnormalities | Intravenous Ganciclovir† 5mg/kg/day (N=175) % | Ganciclovir Capsules‡ 3000mg/day (N=320) %
Neutropenia with Absolute Neutrophil Count (ANC) per µL:
<500 | 25% | 18%
500 - <749 | 14% | 17%
750 - <1000 | 16% | 19%
Anemia with Hemoglobin (g/dL):
<6.5 | 5% | 2%
6.5 - <8.0 | 16% | 10%
8.0 - <9.5 | 26% | 25%
Serum Creatinine (mg/dL):
≥2.5 | 2% | 1%
≥1.5 - <2.5 | 14% | 12%

* Pooled data from treatment studies ICM 1653, ICM 1774, and AVI 034
† Mean time on therapy = 103 days, including allowed re-induction treatment periods
‡ Mean time on therapy = 91 days, including allowed re-induction treatment periods

Adverse Reactions in Transplant Recipients
There have been three controlled clinical trials of intravenous ganciclovir for the prevention of CMV disease in transplant recipients. Selected laboratory abnormalities are summarized in Tables 4 and 5 below. Table 4 shows the frequency of neutropenia and thrombocytopenia and Table 5 shows the frequency of elevated serum creatinine values observed in these trials [see Clinical Studies (14)].

Table 4. Laboratory Abnormalities in Controlled Trials – Transplant Recipients who Received Intravenous Ganciclovir or Placebo
Laboratory Abnormalities | Heart Allograft* |  | Bone Marrow Allograft†
Laboratory Abnormalities | Intravenous Ganciclovir (N=76) | Placebo (n=73) | Intravenous Ganciclovir (n=57) | Control (n=55)
Neutropenia
Absolute Neutrophil Count (ANC) per µL:
<500 | 4% | 3% | 12% | 6%
<500-1000 | 3% | 8% | 29% | 17%
TOTAL ANC; ≤1000/µL | 7% | 11% | 41% | 23%
Thrombocytopenia
Platelet count per µL:
<25,000 | 3% | 1% | 32% | 28%
25,000-50,000 | 5% | 3% | 25% | 37%
TOTAL Platelet Count ≤50,000/µL | 8% | 4% | 57% | 65%

Table 5. Serum Creatinine Levels in Controlled Trials – Transplant Recipients who Received Intravenous Ganciclovir or Placebo
Serum Creatinine Levels (mg/dL) | Heart Allograft ICM 1496 |  | Bone Marrow Allograft ICM 1570 |  | Bone Marrow Allograft ICM 1689
Serum Creatinine Levels (mg/dL) | Intravenous Ganciclovir (N=76) | Placebo (n=73) | Intravenous Ganciclovir (n=20) | Placebo (n=73) | Intravenous Ganciclovir (n=37) | Placebo (n=35)
≥2.5 | 18% | 14% | 20% | 0% | 0% | 0%
≥1.5 - <2.5 | 58% | 69% | 50% | 35% | 43% | 44%

Other Adverse Reactions in Clinical Trials in Patients with CMV Retinitis and in Transplant Recipients
Other adverse reactions with intravenous ganciclovir or ganciclovir capsules in controlled clinical studies in either subjects with AIDS or transplant recipients are listed below [see Clinical Studies (14)]. All these events occurred in at least 3 subjects.

Ear and labyrinth disorders: tinnitus

Eye disorders: abnormal vision, vitreous disorder

Gastrointestinal disorders: enlarged abdomen, aphthous stomatitis, constipation, dyspepsia, eructation, gastrointestinal perforation, pancreatitis, dry mouth

General disorders and administration site conditions: asthenia, injection site inflammation, edema, malaise, multiple organ failure, pain, chest pain

Blood and lymphatic system disorders: pancytopenia

Infections and infestations: sepsis

Investigations: abnormal liver function test, decreased creatinine clearance

Metabolism and nutritional disorders: weight loss

Musculoskeletal and connective tissue disorders: arthralgia, leg cramps, myalgia, myasthenia

Renal and urinary disorders: kidney failure, abnormal kidney function, urinary frequency

Respiratory, thoracic and mediastinal disorders: increased cough, dyspnea

Nervous system disorders: confusion, dizziness, headache, insomnia, seizures, somnolence, abnormal thinking, tremor, taste perversion

Psychiatric disorders: abnormal dreams, anxiety, depression

Skin and subcutaneous disorders: alopecia, dry skin

Vascular disorders: hypertension, phlebitis, vasodilation

6.2 Postmarketing Experience

The following adverse reactions have been identified during post-approval use of intravenous ganciclovir. Because these reactions are reported voluntarily from a population of uncertain size, it is not always possible to reliably estimate their frequency or establish a causal relationship to drug exposure.

Blood and lymphatic system disorders: hemolytic anemia

Cardiac disorders: cardiac arrest, cardiac conduction abnormality, torsades de pointes, ventricular tachycardia

Congenital, familial and genetic disorders: congenital anomaly

Eye disorders: cataracts, dry eyes

Gastrointestinal disorders: intestinal ulceration

Hepatobiliary disorders: hepatic failure, cholestasis, cholelithiasis, hepatitis

Immune system disorders: anaphylactic reaction, allergic reaction, vasculitis

Investigations: increased blood triglycerides, increased blood antidiuretic hormone

Metabolism and nutrition disorders: acidosis, hypercalcemia, hyponatremia

Musculoskeletal and connective tissue disorders: arthritis, rhabdomyolysis

Nervous system disorders: dysesthesia, dysphasia, encephalopathy, extrapyramidal disorder, facial palsy, intracranial hypertension, loss of memory, loss of smell, myelopathy, oculomotor nerve paralysis, stroke

Renal and urinary disorders: hemolytic uremic syndrome, renal tubular disorder

Reproductive system and breast disorders: infertility, testicular hypotrophy

Respiratory, thoracic and mediastinal disorders: bronchospasm, pulmonary fibrosis

Psychiatric disorders: hallucinations, irritability

Skin and subcutaneous tissue disorders: exfoliative dermatitis, Stevens-Johnson syndrome

Vascular disorders: peripheral ischemia

7 DRUG INTERACTIONS

Established and other potentially significant drug interactions conducted with ganciclovir are listed in Table 6 [see Clinical Pharmacology (12.3)].

Table 6. Established and Other Potentially Significant Drug Interactions with Ganciclovir
Name of the Concomitant Drug | Change in the Concentration of Ganciclovir or Concomitant Drug | Clinical Comment
Didanosine | ↑ Didanosine | Patients should be closely monitored for didanosine toxicity.
Zidovudine | ↓ Ganciclovir ↑ Zidovudine | Dose reduction or interruption may be needed because both zidovudine and ganciclovir have the potential to cause neutropenia and anemia. Monitor with frequent tests of white blood cell counts with differential and hemoglobin levels.
Probenecid | ↑ Ganciclovir | GANCICLOVIR INJECTION dose may need to be reduced. Monitor for evidence of ganciclovir toxicity.
Imipenem-cilastatin | Unknown | Coadministration with imipenem-cilastatin is not recommended because generalized seizures have been reported in patients who received ganciclovir and imipenem-cilastatin.
Cyclosporine or amphotericin B | Unknown | Monitor renal function when GANCICLOVIR INJECTION is co-administered with cyclosporine or amphotericin B because of potential increase in serum creatinine [see Warnings and Precautions (5.2)].
Dapsone, pentamidine, flucytosine, vincristine, vinblastine, adriamycin, amphotericin B, trimethoprim/sulfamethoxazole combinations or other nucleoside analogues | Unknown | Co-administration with GANCICLOVIR INJECTION should be considered only if the potential benefits are judged to outweigh the risks because of potential additive toxicity.

8 USE IN SPECIFIC POPULATIONS

8.1 Pregnancy

Risk Summary
Inanimal studies, ganciclovir caused maternal and fetal toxicity and embryo-fetal mortality in pregnant mice and rabbits as well as teratogenicity in rabbits at exposures two times the exposure at the recommended human dose (RHD) [see Data]. Although placental transfer of ganciclovir has been shown to occur based on ex vivo experiments with human placenta and on at least one case report in a pregnant woman, no adequate human data are available to establish whether GANCICLOVIR INJECTION poses a risk to pregnancy outcomes. The background risk of major birth defects and miscarriage for the indicated population is unknown. In the U.S. general population, the estimated background risk of major birth defects and miscarriage in the clinically recognized pregnancies is 2-4% and 15−20%, respectively.

Clinical considerations

Disease-associated maternal and/or fetal risk

Most maternal CMV infections are subclinical or they may be associated with a mononucleosis-like syndrome. However, in immunocompromised patients, CMV infections are often symptomatic and are associated with significant morbidity and mortality. The transmission of CMV to the fetus is a result of maternal viremia and transplacental infection. CMV infection can also occur perinatally from mother to infant by exposure to CMV in cervicovaginal secretions. Approximately 10% of infected newborns are symptomatic at birth. Mortality in symptomatic infants is about 10%, and approximately 50 to 90% of survivors experience significant problems, including sensorineural hearing loss, mental retardation, and other neurologic deficits. The risk and severity of congenital CMV infection appear to be higher in infants born to mothers with primary CMV infection than in those born to mothers with reactivation of CMV infection.

Data

Animal Data

Daily intravenous doses of ganciclovir were administered to pregnant mice (108 mg/kg/day) and rabbits (60 mg/kg/day), and also to female mice (90 mg/kg) prior to mating, during gestation, and during lactation. Fetal resorptions were present in at least 85% of rabbits and mice. Additional effects observed in rabbits included fetal growth retardation, embryolethality, teratogenicity, and/or maternal toxicity. Teratogenic changes included cleft palate, anophthalmia/microphthalmia, aplastic organs (kidney and pancreas), hydrocephaly and brachygnathia. In pre/postnatal development studies in mice, there were maternal/fetal toxicity and embryolethality which included fetal effects of hypoplasia of the testes and seminal vesicles in the male offspring, as well as pathologic changes in the nonglandular region of the stomach. The systemic exposure (AUC) of ganciclovir during these studies was approximately 2-times (pregnant mice and rabbits) and 1.7-times (pre/postnatal mice) the exposure in humans at the RHD [see Nonclinical Toxicology (13.1)].

8.2 Lactation

Risk Summary
No data are available regarding the presence of ganciclovir in human milk, the effects on the breastfed infant, or the effects on milk production. When ganciclovir was administered to lactating rats, ganciclovir was present in milk [see Data]. Advise nursing mothers that breastfeeding is not recommended during treatment with GANCICLOVIR INJECTION because of the potential for serious adverse reactions in nursing infants. Furthermore, the Centers for Disease Control and Prevention recommends that HIV-infected mothers not breastfeed their infants to avoid potential postnatal transmission of HIV [see Warnings and Precautions (5.1, 5.3, 5.5), Nonclinical Toxicology (13.1)].

Data

Animal Data

Ganciclovir administered intravenously (at 0.13 mg/h) to lactating rats (on lactation day 15) resulted in passive transfer into milk. The milk-to-serum ratio for ganciclovir at steady state was 1.6 ± 0.33.

8.3 Females and Males of Reproductive Potential

Pregnancy Testing
Females of reproductive potential should undergo pregnancy testing before initiation of GANCICLOVIR INJECTION [see Dosage and Administration (2.2), Use in Specific Populations (8.1)].

Contraception

Females

Because of the mutagenic and teratogenic potential of ganciclovir, females of reproductive potential should be advised to use effective contraception during treatment and for at least 30 days following treatment with GANCICLOVIR INJECTION [see Warnings and Precautions (5.3, 5.4), Nonclinical Toxicology (13.1)].

Males

Because of its mutagenic potential, males should be advised to practice barrier contraception during and for at least 90 days following, treatment with GANCICLOVIR INJECTION [see Warnings and Precautions (5.3, 5.4), Nonclinical Toxicology (13.1)].

Infertility
GANCICLOVIR INJECTION at the recommended doses may cause temporary or permanent female and male infertility [see Warnings and Precautions (5.3, 5.4), Nonclinical Toxicology (13.1)].

8.4 Pediatric Use

Safety and efficacy of GANCICLOVIR INJECTION have not been established in pediatric patients.

A total of 120 pediatric patients with serious CMV infections participated in clinical trials. Granulocytopenia and thrombocytopenia were the most common adverse reactions.

The pharmacokinetic characteristics of ganciclovir administered intravenously were studied in 27 neonates (aged 2 to 49 days) and 10 pediatric patients, aged 9 months to 12 years. In neonates, the pharmacokinetic parameters after ganciclovir intravenous doses of 4 mg/kg (n=14) and 6 mg/kg (n=13) were Cmax 5.5 ± 1.6 and 7.0 ± 1.6 μg/mL, systemic clearance 3.14 ± 1.75 and 3.56 ± 1.27 mL/min/kg, and t1/2 of 2.4 hours (harmonic mean) for both doses, respectively.

In pediatric patients 9 months to 12 years of age, the pharmacokinetic characteristics of ganciclovir were the same after single and multiple (every 12 hours) intravenous doses (5 mg/kg). The steady-state volume of distribution was 0.64 ± 0.22 L/kg, Cmax was 7.9 ± 3.9 μg/mL, systemic clearance was 4.7 ± 2.2 mL/min/kg, and t1/2 was 2.4 ± 0.7 hours.

Although the pharmacokinetics of intravenous ganciclovir in pediatric patients were similar to those observed in adults, the safety and efficacy of ganciclovir at these exposures in pediatric patients have not been established.

8.5 Geriatric Use

Clinical studies of ganciclovir did not include sufficient numbers of subjects aged 65 and over to determine whether they respond differently from younger subjects. In general, dose selection for an elderly patient should be cautious, reflecting the greater frequency of decreased hepatic, renal, or cardiac function, and of concomitant disease or other drug therapy. Ganciclovir is known to be substantially excreted by the kidney, and the risk of toxic reactions to this drug may be greater in patients with impaired renal function. Because elderly patients are more likely to have decreased renal function, care should be taken in dose selection. In addition, renal function should be monitored and dosage adjustments should be made accordingly [see Dosage and Administration (2.5), Warnings and Precautions (5.2), Use in Specific Populations (8.6)].

8.6 Renal Impairment

Dose reduction is recommended when administering GANCICLOVIR INJECTION to patients with renal impairment [see Dosage and Administration (2.5), Warnings and Precautions (5.2), Adverse Reactions (6.1)].

Hemodialysis has been shown to reduce plasma levels of ganciclovir by approximately 50%.

8.7 Hepatic Impairment

The safety and efficacy of ganciclovir have not been studied in patients with hepatic impairment.

10 OVERDOSAGE

Adverse reactions reported with overdosage of intravenous ganciclovir included irreversible pancytopenia, acute renal failure requiring hemodialysis, neutropenia, thrombocytopenia, hepatitis, and seizures.

Since ganciclovir is dialyzable, dialysis may be useful in reducing serum concentrations. Adequate hydration should be maintained. The use of hematopoietic growth factors should be considered in patients with cytopenias [see Dosage and Administration (2.5), Warnings and Precautions (5.1)].

11 DESCRIPTION

GANCICLOVIR INJECTION, 500 mg is a sterile, unpreserved solution for intravenous administration. The appearance of the solution is clear and colorless. Each mL contains 2.0 mg of ganciclovir, 8.0 mg of sodium chloride in water for injection, and may contain sodium hydroxide, and/or hydrochloric acid, as required to adjust the pH to 7.5.

Ganciclovir, an antiviral agent, is a synthetic guanine derivative, 9-[[2-hydroxy-1-(hydroxymethyl)- ethoxy]methyl]guanine. Ganciclovir is a white to off-white crystalline powder with a molecular formula of C9 H13 N5 04 and a molecular weight of 255.23. Ganciclovir is a polar hydrophilic compound with a solubility of 2.6 mg/mL in water at 25°C and an n-octanol/water partition coefficient of 0.022. The pKa s for ganciclovir are 2.2 and 9.4.

The chemical structure of ganciclovir is:

The plastic container is fabricated from a multilayer film designed for medical use. The solution is in contact with the inner polypropylene layer of the container. No components of the plastic container material were found to migrate into the solution.

12 CLINICAL PHARMACOLOGY

12.1 Mechanism of Action

Ganciclovir is an antiviral drug with activity against cytomegalovirus (CMV) [see Microbiology (12.4)].

12.3 Pharmacokinetics

Absorption:
At the end of a 1-hour intravenous infusion of 5 mg/kg ganciclovir, total AUC ranged between 22.1 ±3.2 (n=16) and 26.8 ± 6.1 g·hr/mL (n=16) and Cmax ranged between 8.27 ± 1.02 (n=16) and 9.0 ± 1.4 g/mL (n=16).

Distribution:
The steady-state volume of distribution of ganciclovir after intravenous administration was 0.74 ± 0.15 L/kg (n=98). Cerebrospinal fluid concentrations obtained 0.25 to 5.67 hours post-dose in 3 patients who received 2.5 mg/kg ganciclovir intravenously every 8 hours or every 12 hours ranged from 0.31 to 0.68 g/mL representing 24% to 70% of the respective plasma concentrations. Binding to plasma proteins was 1% to 2% over ganciclovir concentrations of 0.5 and 51 g/mL.

Elimination:
Renal excretion of unchanged drug by glomerular filtration and active tubular secretion is the major route of elimination of ganciclovir. In patients with normal renal function, 91.3 ± 5.0% (n=4) of intravenously administered ganciclovir was recovered unchanged in the urine. Systemic clearance of intravenously administered ganciclovir was 3.52 ± 0.80 mL/min/kg (n=98) while renal clearance was 3.20 ± 0.80 mL/min/kg (n=47), accounting for 91 ± 11% of the systemic clearance (n=47). Following intravenous administration, ganciclovir half-life was 3.5 ± 0.9 hours (n=98) with linear pharmacokinetics over the dose range of 1.6 to 5.0 mg/kg.

Specific Populations

Patients with Renal Impairment

The pharmacokinetics of ganciclovir following intravenous administration of ganciclovir were evaluated in 10 immunocompromised patients with renal impairment who received doses ranging from 1.25 to 5.0 mg/kg (Table 7). Hemodialysis reduces plasma concentrations of ganciclovir by about 50% after intravenous administration.

Table 7. Pharmacokinetics of Ganciclovir in Patients with Renal Impairment
Estimated; Creatinine; Clearance; (mL/min) | n | Dose | Clearance; (mL/min); Mean ± SD | Half-life; (hours); Mean ± SD
50-79 | 4 | 3.2-5 mg/kg | 128 ± 63 | 4.6 ± 1.4
25-49 | 3 | 3-5 mg/kg | 57 ± 8 | 4.4 ± 0.4
<25 | 3 | 1.25-5 mg/kg | 30 ± 13 | 10.7 ± 5.7

Race (Ethnicity) and Gender
The effects of race/ethnicity and gender were studied in subjects receiving a dose regimen of 1000 mg every 8 hours. Although the numbers of Blacks (16%) and Hispanics (20%) were small, there appeared to be a trend towards a lower steady-state Cmax and AUC0-8 in these subpopulations as compared to Caucasians. No definitive conclusions regarding gender differences could be made because of the small number of females (12%); however, no differences between males and females were observed.

Drug Interactions

Didanosine

When the standard intravenous ganciclovir induction dose (5 mg/kg infused over 1 hour every 12 hours) was coadministered with didanosine at a dose of 200 mg orally every 12 hours, the steady-state didanosine AUC0-12 increased 70 ± 40% (range: 3% to 121%, n=11) and Cmax increased 49 ± 48% (range: -28% to 125%). In a separate study, when the standard intravenous ganciclovir maintenance dose (5 mg/kg infused over 1 hour every 24 hours) was coadministered with didanosine at a dose of 200 mg orally every 12 hours, didanosine AUC0-12 increased 50 ± 26% (range: 22% to 110%, n=11) and Cmax increased 36 ± 36% (range: -27% to 94%) over the first didanosine dosing interval. Ganciclovir pharmacokinetics were not affected by didanosine. In both studies, there was no significant change in the renal clearance of either drug.

Zidovudine

At an oral dose of 1000 mg of ganciclovir every 8 hours, mean steady-state ganciclovir AUC0-8

decreased 17 ± 25% (range: -52% to 23%) in the presence of zidovudine, 100 mg every 4 hours (n=12). Steady-state zidovudine AUC0-4 increased 19 ± 27% (range: -11% to 74%) in the presence of ganciclovir. No drug-drug interaction studies have been conducted with intravenous ganciclovir and zidovudine.

Probenecid

At an oral dose of 1000 mg of ganciclovir every 8 hours (n=10), ganciclovir AUC0-8 increased 53 ± 91% (range: -14% to 299%) in the presence of probenecid, 500 mg every 6 hours. Renal clearance of ganciclovir decreased 22 ± 20% (range: -54% to -4%), which is consistent with an interaction involving competition for renal tubular secretion. No drug-drug interaction studies have been conducted with intravenous ganciclovir and probenecid.

Cyclosporine

In a retrospective analysis of 93 liver allograft recipients receiving ganciclovir (5 mg/kg infused over 1 hour every 12 hours) and oral cyclosporine (at therapeutic doses), there was no evidence of an effect on cyclosporine whole blood concentrations.

12.4 Microbiology

Antiviral Activity
Thciclovir is a synthetic analogue of 2'-deoxyguanosine, which inhibits replication of human CMV in cell culture and in vivo. In CMV-infected cells, ganciclovir is initially phosphorylated to ganciclovir monophosphate by the viral protein kinase, pUL97. Further phosphorylation occurs by cellular kinases to produce ganciclovir triphosphate, which is then slowly metabolized intracellularly. As the phosphorylation is largely dependent on the viral kinase, phosphorylation of ganciclovir occurs preferentially in virus-infected cells. The virustatic activity of ganciclovir is due to inhibition of the viral DNA polymerase, pUL54, by ganciclovir triphosphate.

Antiviral Activity
The median concentration of ganciclovir that inhibits CMV replication (EC50 value) in cell culture (laboratory strains or clinical isolates) has ranged from 0.08 to 13.6 micromolar (0.02 to 3.48 μg/mL). Ganciclovir inhibits mammalian cell proliferation (CC50 value) in cell culture at higher concentrations ranging from 118 to 2840 micromolar (30 to 725 μg/mL). Bone marrow-derived colony-forming cells are more sensitive [CC50 value = 0.1 to 2.7 micromolar (0.028 to 0.7 μg/mL)]. The relationship between the antiviral activity in cell culture and clinical response has not been established.

Resistance
Cell Culture: CMV isolates with reduced susceptibility to ganciclovir have been selected in cell culture. Growth of CMV strains in the presence of ganciclovir resulted in the selection of amino acid substitutions in the viral protein kinase pUL97 and the viral DNA polymerase pUL54.

In vivo: Viruses resistant to ganciclovir can arise after prolonged treatment or prophylaxis with ganciclovir by selection of substitutions in pUL97 and/or pUL54. Limited clinical data are available on the development of clinical resistance to ganciclovir and many pathways to resistance exist. The possibility of viral resistance should be considered in patients who show poor clinical response or experience persistent viral excretion during therapy.

CMV resistance to ganciclovir has been observed in individuals with AIDS and CMV retinitis who have never received ganciclovir therapy. Viral resistance has also been observed in patients receiving prolonged treatment for CMV retinitis with ganciclovir. In a controlled study of oral ganciclovir for prevention of AIDS-associated CMV disease, 364 individuals had one or more cultures performed after at least 90 days of ganciclovir treatment. Of these, 113 had at least one positive culture. The last available isolate from each subject was tested for reduced sensitivity, and 2 of 40 were found to be resistant to ganciclovir. These resistant isolates were associated with subsequent treatment failure for retinitis.

13 NONCLINICAL TOXICOLOGY

13.1 Carcinogenesis, Mutagenesis, Impairment of Fertility

Carcinogenesis, Mutagenesis
Ganciclovir was carcinogenic in mice at the same mean drug exposure in humans as at the RHD (5 mg/kg). At the dose of 1000 mg/kg/day (1.4 times the exposure at the RHD) there was a significant increase in the incidence of tumors of the preputial gland in males, forestomach (nonglandular mucosa) in males and females, and reproductive tissues (ovaries, uterus, mammary gland, clitoral gland and vagina) and liver in females. At the dose of 20 mg/kg/day (0.1 times the exposure at the RHD), a slightly increased incidence of tumors was noted in the preputial and harderian glands in males, forestomach in males and females, and liver in females. No carcinogenic effect was observed in mice administered ganciclovir at 1 mg/kg/day (exposure estimated as 0.01 times the RHD). Except for histiocytic sarcoma of the liver, ganciclovir-induced tumors were generally of epithelial or vascular origin. Although the preputial and clitoral glands, forestomach and harderian glands of mice do not have human counterparts, ganciclovir should be considered a potential carcinogen in humans.

Ganciclovir increased mutations in mouse lymphoma cells and DNA damage in human lymphocytes in vitro at concentrations of 50 to 500 and 250 to 2000 μg/mL, respectively. In the mouse micronucleus assay, ganciclovir was clastogenic at doses of 150 and 500 mg/kg (2.8 to 10 times the exposure at the RHD) but not at doses of 50 mg/kg (exposure approximately comparable to the RHD). Ganciclovir was not mutagenic in the Ames Salmonella assay at concentrations of 500 to 5000 μg/mL.

Impairment of Fertility
Ganciclovir caused decreased mating behavior, decreased fertility, and an increased incidence of embryolethality in female mice following doses of 90 mg/kg/day (exposures approximately 1.7 times the RHD). Ganciclovir caused decreased fertility in male mice and hypospermatogenesis in mice and dogs following daily oral or intravenous administration of doses ranging from 0.2 to 10 mg/kg. Systemic drug exposure (AUC) at the lowest dose showing toxicity in each species ranged from 0.03 to 0.1 times the exposure at the RHD.

14 CLINICAL STUDIES

14.1 Treatment of CMV Retinitis

In a retrospective, non-randomized, single-center analysis of 41 patients with AIDS and CMV retinitis diagnosed by ophthalmologic examination between August 1983 and April 1988, treatment with intravenous ganciclovir resulted in a delay in mean (median) time to first retinitis progression compared to untreated controls [105 (71) days from diagnosis vs. 35 (29) days from diagnosis]. Patients in this series received induction treatment of intravenous ganciclovir 5 mg/kg twice daily for 14 to 21 days followed by maintenance treatment with either 5 mg/kg once daily, 7 days per week or 6 mg/kg once daily, 5 days per week.

In a controlled, randomized trial conducted between February 1989 and December 1990, immediate treatment with intravenous ganciclovir was compared to delayed treatment in 42 patients with AIDS and peripheral CMV retinitis; 35 of 42 patients (13 in the immediate-treatment group and 22 in the delayed-treatment group) were included in the analysis of time to retinitis progression. Based on masked assessment of fundus photographs, the mean [95% CI] and median [95% CI] times to progression of retinitis were 66 days [39, 94] and 50 days [40, 84], respectively, in the immediate-treatment group compared to 19 days [11, 27] and 13.5 days [8, 18], respectively, in the delayed-treatment group.

Data from trials ICM 1653, ICM 1774, and AVI034, which were performed comparing intravenous to oral ganciclovir for treatment of CMV retinitis in patients with AIDS, are shown in Table 8, and Figures 1, 2, and 3, and are discussed below.

Table 8. Population Characteristics in Studies ICM 1653, ICM 1774 and AVI 034
 |  | ICM 1653 (n=121) | ICM 1774 (n=225) | AVI 034 (n=159)
Median age (years) |  | 38 | 37 | 39
Range |  | 24-62 | 22-56 | 23-62
Sex | Males | 116 (96%) | 222 (99%) | 148 (93%)
Sex | Females | 5 (4%) | 3 (1%) | 10 (6%)
 | Asian | 3 (3%) | 5 (2%) | 7 (4%)
Ethnicity | Black | 11 (9%) | 9 (4%) | 3 (2%)
Ethnicity | Caucasian | 98 (81%) | 186 (83%) | 140 (88%)
 | Other | 9 (7%) | 25 (11%) | 8 (5%)
Median CD4 Count |  | 9.5 | 7.0 | 10.0
Range |  | 0-141 | 0-80 | 0-320
Mean (SD) Observation Time (days) |  | 107.9 (43.0) | 97.6 (42.5) | 80.9 (47.0)

Trial ICM 1653

In this randomized, open-label, parallel group trial, conducted between March 1991 and November1992, patients with AIDS and newly diagnosed CMV retinitis received a 3-week induction course of intravenous ganciclovir, 5 mg/kg twice daily for 14 days followed by 5 mg/kg once daily for 1 additional week. Following the 21-day intravenous induction course, patients with stable CMV retinitis were randomized to receive 20 weeks of maintenance treatment with either intravenous ganciclovir, 5 mg/kg once daily, or ganciclovir capsules, 500 mg 6 times daily (3000 mg/day). The study showed that the mean [95% CI] and median [95% CI] times to progression of CMV retinitis, as assessed by masked reading of fundus photographs, were 57 days [44, 70] and 29 days [28, 43], respectively, for patients on oral therapy compared to 62 days [50, 73] and 49 days [29, 61], respectively, for patients on intravenous therapy. The difference [95% CI] in the mean time to progression between the oral and intravenous therapies (oral - IV) was -5 days [-22, 12]. See Figure 1 for comparison of the proportion of patients remaining free of progression over time.

Trial ICM 1774

In this three-arm, randomized, open-label, parallel group trial, conducted between June 1991 and August 1993, patients with AIDS and stable CMV retinitis following from 4 weeks to 4 months of treatment with intravenous ganciclovir were randomized to receive maintenance treatment with intravenous ganciclovir, 5 mg/kg once daily, ganciclovir capsules, 500 mg 6 times daily, or ganciclovir capsules, 1000 mg three times daily for 20 weeks. The study showed that the mean [95% CI] and median [95% CI] times to progression of CMV retinitis, as assessed by masked reading of fundus photographs, were 54 days [48, 60] and 42 days [31, 54], respectively, for patients on oral therapy compared to 66 days [56, 76] and 54 days [41, 69], respectively, for patients on intravenous therapy. The difference [95% CI] in the mean time to progression between the oral and intravenous therapies (oral - IV) was -12 days [-24, 0]. See Figure 2 for comparison of the proportion of patients remaining free of progression over time.

Trial AVI 034

In this randomized, open-label, parallel group trial, conducted between June 1991 and February 1993, patients with AIDS and newly diagnosed (81%) or previously treated (19%) CMV retinitis who had tolerated 10 to 21 days of induction treatment with intravenous ganciclovir, 5 mg/kg twice daily, were randomized to receive 20 weeks of maintenance treatment with either ganciclovir capsules, 500 mg 6 times daily or intravenous ganciclovir, 5 mg/kg/day. The mean [95% CI] and median [95% CI] times to progression of CMV retinitis, as assessed by masked reading of fundus photographs, were 51 days [44, 57] and 41 days [31, 45], respectively, for patients on oral therapy compared to 62 days [52, 72] and 60 days [42, 83], respectively, for patients on intravenous therapy. The difference [95% CI] in the mean time to progression between the oral and intravenous therapies (oral - IV) was -11 days [-24, 1]. See Figure 3 for comparison of the proportion of patients remaining free of progression over time.

Comparison of other CMV retinitis outcomes between oral and intravenous formulations (development of bilateral retinitis, progression into Zone 1, and deterioration of visual acuity), while not definitive, showed no marked differences between treatment groups in these studies. Because of low event rates among these endpoints, these studies are underpowered to rule out significant differences in these endpoints.

Figure 1. ICM 1653: Time to Progression of CMV Retinitis

Figure 2. ICM 1774: Time to Progression of CMV Retinitis

Figure 3. AVI 034: Time to Progression of CMV Retinitis

14.2 Prevention of CMV Disease in Transplant Recipients

Intravenous ganciclovir was evaluated in three randomized, controlled trials of prevention of CMV disease in organ transplant recipients.

Trial ICM 1496

In a randomized, double-blind, placebo-controlled study of 149 heart transplant recipients at risk for CMV infection (CMV seropositive or a seronegative recipient of an organ from a CMV seropositive donor), there was a reduction in the overall incidence of CMV disease in patients treated with intravenous ganciclovir. Immediately post-transplant, patients received intravenous ganciclovir 5 mg/kg twice daily for 14 days followed by 6 mg/kg once daily for 5 days/week for an additional 14 days. Twelve of the 76 (16%) patients treated with intravenous ganciclovir vs. 31 of the 73 (43%) placebo-treated patients developed CMV disease during the 120-day post-transplant observation period. No significant differences in hematologic toxicities were seen between the two treatment groups [see Adverse Reactions (6.1)].

Trial ICM 1689

In a randomized, double-blind, placebo-controlled study of 72 bone marrow transplant recipients with asymptomatic CMV infection (CMV positive culture of urine, throat or blood) there was a reduction in the incidence of CMV disease in patients treated with intravenous ganciclovir following successful hematopoietic engraftment. Patients with virologic evidence of CMV infection received intravenous ganciclovir 5 mg/kg twice daily for 7 days followed by 5 mg/kg once daily through day 100 post-transplant. One of the 37 (3%) patients treated with intravenous ganciclovir vs 15 of the 35 (43%) placebo-treated patients developed CMV disease during the study. At 6 months post-transplant, there continued to be a reduction in the incidence of CMV disease in patients treated with intravenous ganciclovir. Six of 37 (16%) patients treated with intravenous ganciclovir vs 15 of the 35 (43%) placebo-treated patients developed disease through 6 months post-transplant. The overall rate of survival was higher in the group treated with intravenous ganciclovir, both at day 100 and day 180 post-transplant. Although the differences in hematologic toxicities were not statistically significant, the incidence of neutropenia was higher in the group treated with intravenous ganciclovir [see Dosage and Administration (2.4), Adverse Reactions (6.1)].

Trial ICM 1570

This was a randomized, unblinded trial which evaluated 40 allogeneic bone marrow transplant recipients at risk for CMV disease. Patients underwent bronchoscopy and bronchoalveolar lavage (BAL) on day 35 post-transplant. Patients with histologic, immunologic or virologic evidence of CMV infection in the lung were then randomized to observation or treatment with intravenous ganciclovir (5 mg/kg twice daily for 14 days followed by 5 mg/kg once daily 5 days/week until day 120). Four of 20 (20%) patients treated with intravenous ganciclovir and 14 of 20 (70%) control patients developed interstitial pneumonia. The incidence of CMV disease was lower in the group treated with intravenous ganciclovir [see Dosage and Administration (2.4)].

15 REFERENCES

1. “OSHA Hazardous Drugs.” OSHA. http://www.osha.gov/SLTC/hazardousdrugs/index.html.

16 HOW SUPPLIED/STORAGE AND HANDLING

GANCICLOVIR INJECTION is supplied as a sterile, unpreserved, colorless solution in a single-dose polymeric bag containing 500 mg ganciclovir in 250 mL of solution (2 mg/mL) sealed with a Twist Off port from Technoflex, and oversealed in an aluminum pouch (NDC 51754-2500-1), in cases of 10 (NDC 51754-2500-3). Follow guidelines for handling and disposal for cytotoxic drugs.^1

The premix flexible plastic container bag contains no preservative; any unused portion should be discarded [see Dosage and Administration (2.6)].

Gently shaking should redissolve any crystals that may have formed during transportation and/or storage at temperatures lower than recommended. The solution must be clear at the time of use.

Storage

Store at 20°C to 25°C (68°F to 77°F); excursions permitted to 15° to 30°C (59° to 86°F) [see USP Controlled Room Temperature].

17 PATIENT COUNSELING INFORMATION

Hematologic Toxicity
Inform patients of the potential for hematologic toxicity associated with the use of GANCICLOVIR INJECTION including granulocytopenia (neutropenia), anemia and thrombocytopenia. Inform patients that their blood counts will be closely monitored while on therapy [see Warnings and Precautions (5.1)].

Impairment of Renal Function
Inform patients that ganciclovir has been associated with decreased renal function and that serum creatinine or creatinine clearance will be monitored carefully to allow for dosage adjustment in patients with renal impairment [see Dosage and Administration (2.5), Warnings and Precautions (5.2)].

Impairment of Fertility
Inform patients that ganciclovir has caused decreased fertility in animals and may cause temporary or permanent infertility in humans [see Warnings and Precautions (5.3), Use in Specific Populations (8.3)].

Pregnancy and Contraception
Inform women of childbearing potential that ganciclovir causes birth defects in animals. Advise female patients to use effective contraception during treatment and for at least 30 days following treatment with GANCICLOVIR INJECTION. Similarly, advise men to practice barrier contraception during and for at least 90 days following treatment with GANCICLOVIR INJECTION [see Warnings and Precautions (5.3), Use in Specific Populations (8.1, 8.3)].

Carcinogenicity
Inform patients that ganciclovir causes tumors in animals. Although there is no information from human studies, ganciclovir should be considered a potential carcinogen [see Warnings and Precautions (5.5)].

Drug Interactions
Inform patients that GANCICLOVIR INJECTION may interact with other drugs. Advise patients to report to their healthcare provider the use of any other medication [see Drug Interactions (7)].

Ophthalmological Examination in Patients with CMV Retinitis
Advise patients with CMV retinitis to have frequent ophthalmological examinations while being treated with GANCICLOVIR INJECTION to monitor disease status and for other retinal abnormalities. More frequent ophthalmological follow-up may be needed in some cases [see Dosage and Administration (2.2), Adverse Reactions (6.1)].

Lactation
Advise nursing mothers that breastfeeding is not recommended during treatment with GANCICLOVIR INJECTION because of the potential for serious adverse events in nursing infants and because HIV can be passed to the baby in breast milk [see Use in Specific Populations (8.2)].

Manufactured and distributed by:

Exela Pharma Sciences

Lenoir, NC 28645

Principal Display Panel

NDC 51754-2500-1 250 mL

GANCICLOVIR INJECTION

500 mg per 250 mL (2 mg per mL)

0.8% sodium chloride solution

Single-dose for intravenous use only

Discard unused portion of drug

Bag Overwrap Label